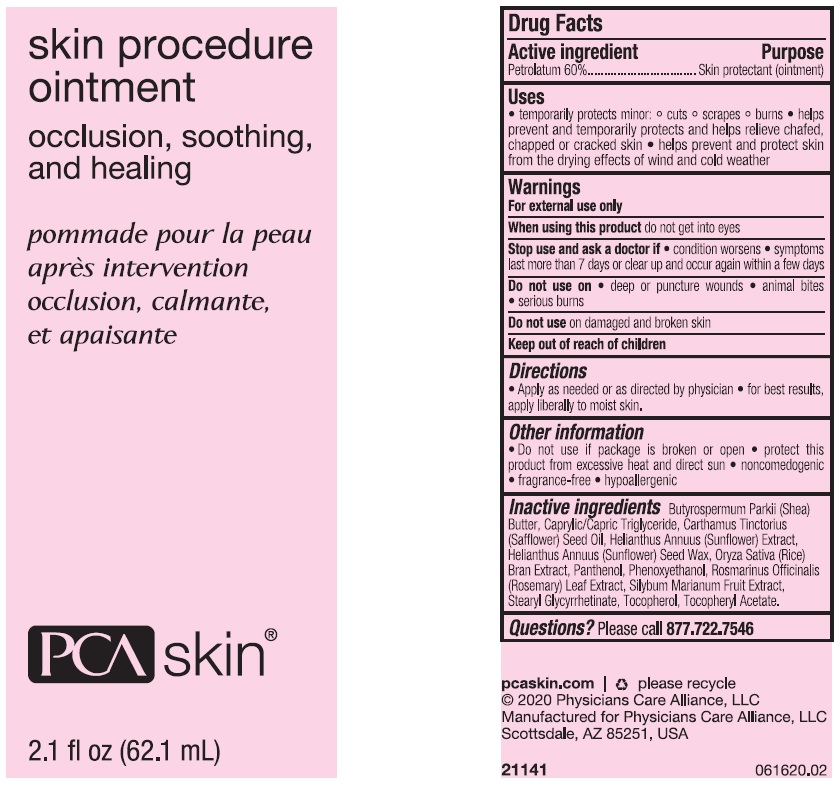 DRUG LABEL: PCA Skin Skin Procedure
NDC: 68726-680 | Form: OINTMENT
Manufacturer: CP Skin Health Group, Inc.
Category: otc | Type: HUMAN OTC DRUG LABEL
Date: 20230130

ACTIVE INGREDIENTS: PETROLATUM 600 mg/1 mL
INACTIVE INGREDIENTS: SHEA BUTTER; MEDIUM-CHAIN TRIGLYCERIDES; SAFFLOWER OIL; HELIANTHUS ANNUUS FLOWERING TOP; HELIANTHUS ANNUUS SEED WAX; RICE BRAN; PANTHENOL; PHENOXYETHANOL; ROSEMARY; MILK THISTLE; STEARYL GLYCYRRHETINATE; TOCOPHEROL; .ALPHA.-TOCOPHEROL ACETATE

PCA Skin Skin Procedure Ointment

Active ingredient

Petrolatum 60%

Purpose

Skin protectant (ointment)

Uses

• temporarily protects minor: º cuts º scrapes º burns • helps prevent and temporarily protects and helps relieve chafed, chapped or cracked skin • helps prevent and protect skin from the drying effects of wind and cold weather

Warnings

For external use only

When using this product

do not get into eyes

Stop use and ask a doctor if

- condition worsens
- symptoms last more than 7 days or clear up and occur again within a few days

Do not use on

- deep or puncture wounds
- animal bites
- serious burns

Do not use on damaged and broken skin

Directions

- Apply as needed or as directed by physician
- for best results, apply liberally to moist skin.

Other information

- Do not use if package is broken or open
- protect this product from excessive heat and direct sun
- noncomedogenic
- fragrance-free
- hypoallergenic

Inactive ingredients

Butyrospermum Parkii (Shea) Butter, Caprylic/Capric Triglyceride, Carthamus Tincotirius (Safflower) Seed Oil, Helianthus Annuus (Sunflower) Extract, Helianthus Annuus (Sunflower) Seed Wax, Oryza Sativa (Rice) Bran Extract, Panthenol, Phenoxyethanol, Rosamarinus Officinalis (Rosemary) Leaf Extract, Silybum Marianum Fruit Extract, Stearyl Glycyrrhetinate, Tocopherol, Tocopheryl Acetate.

Questions?

Please call 877.722.7546